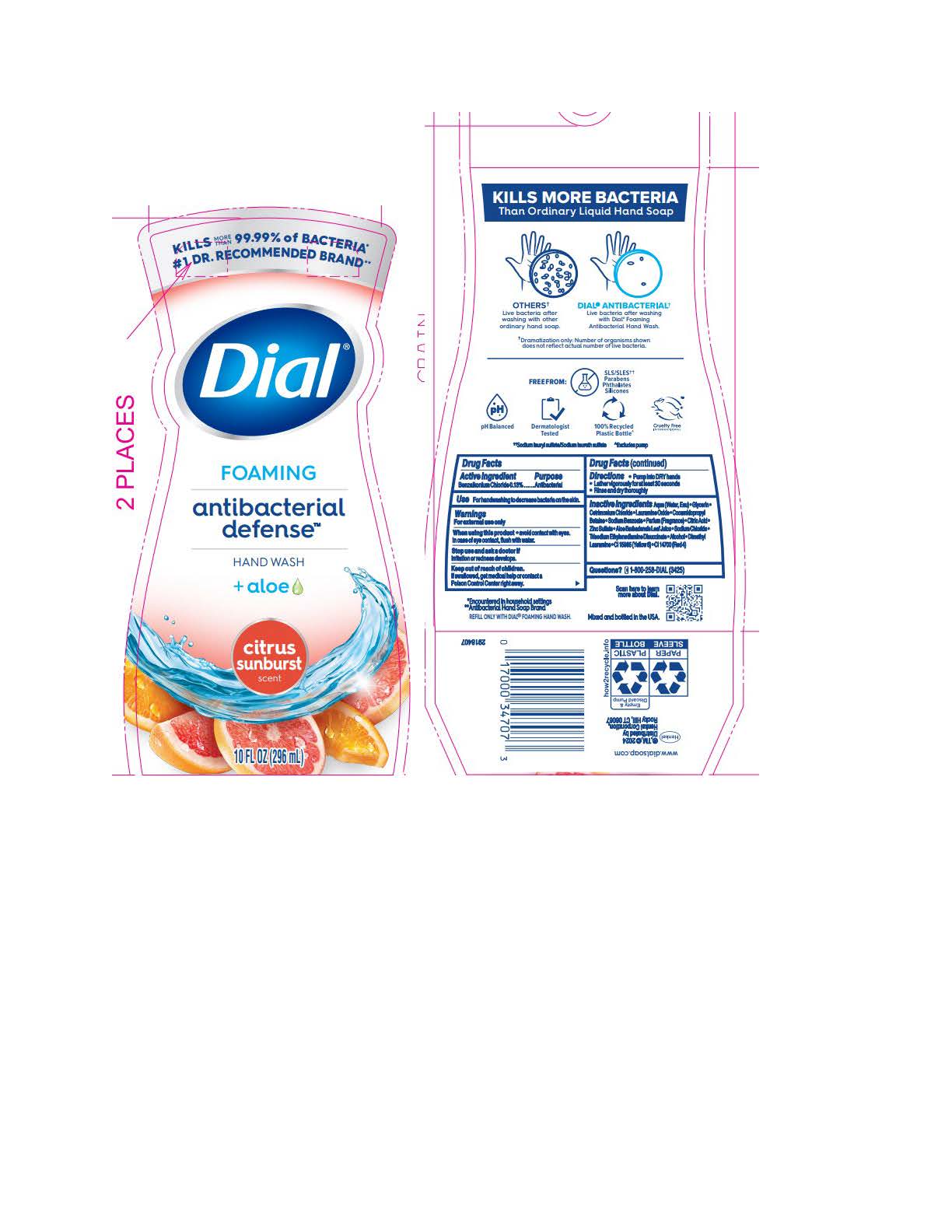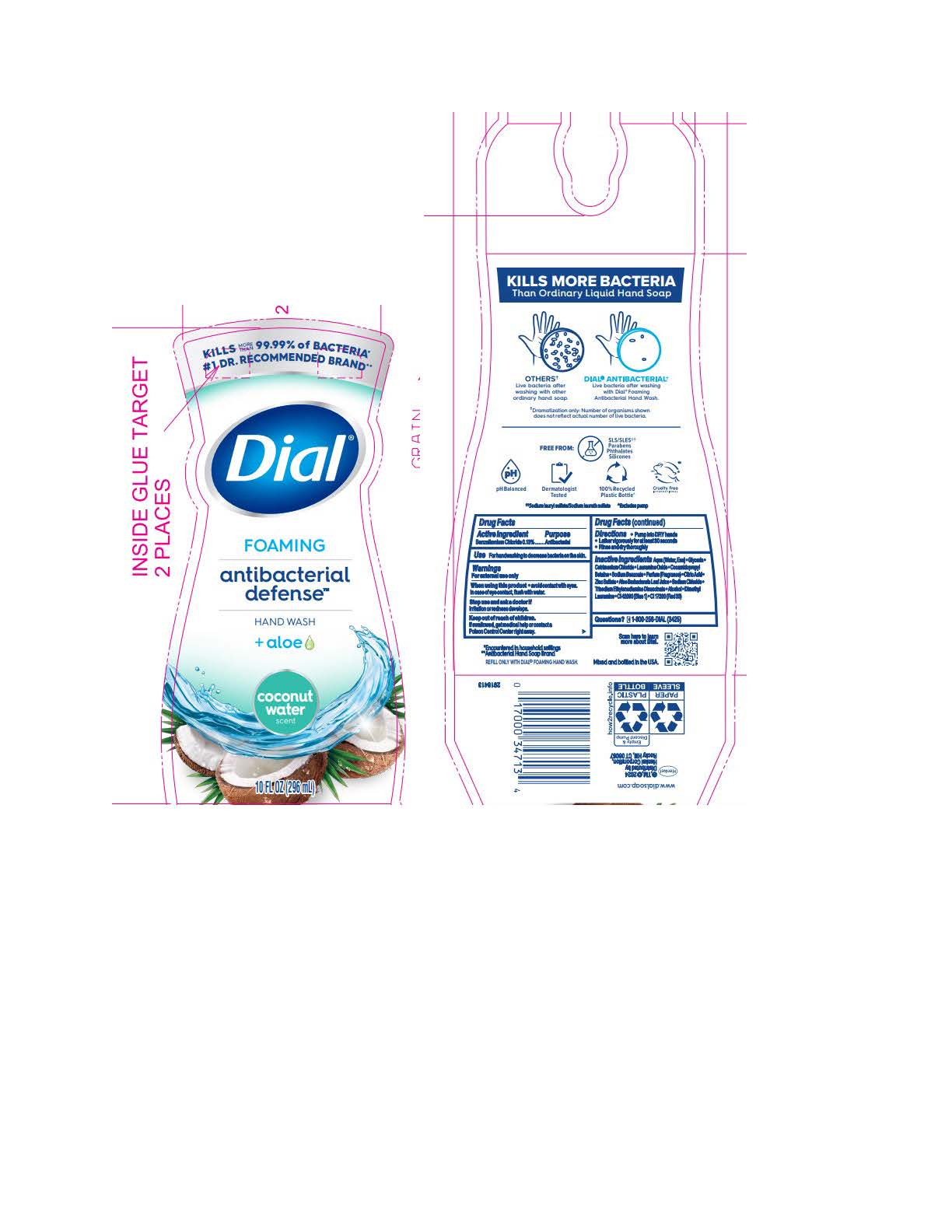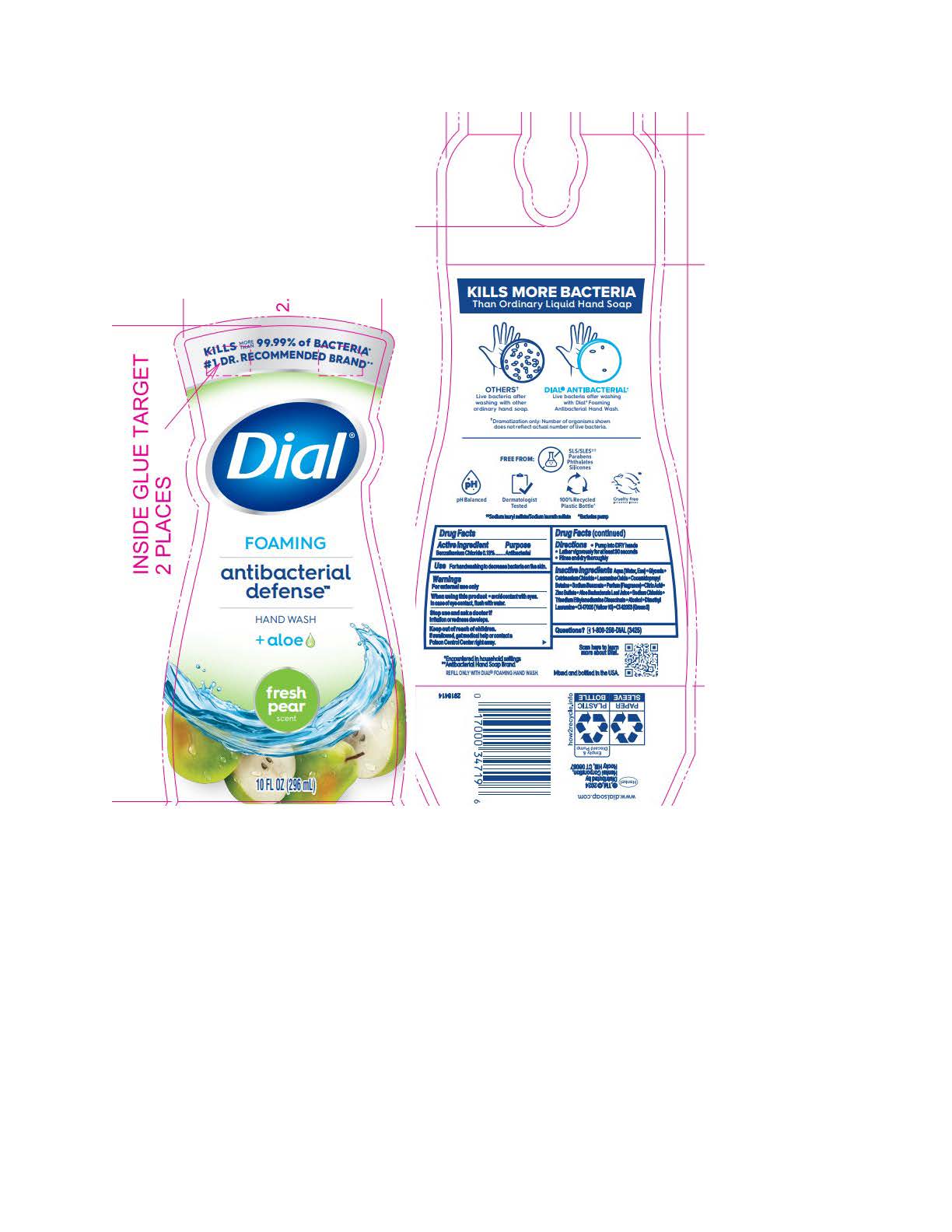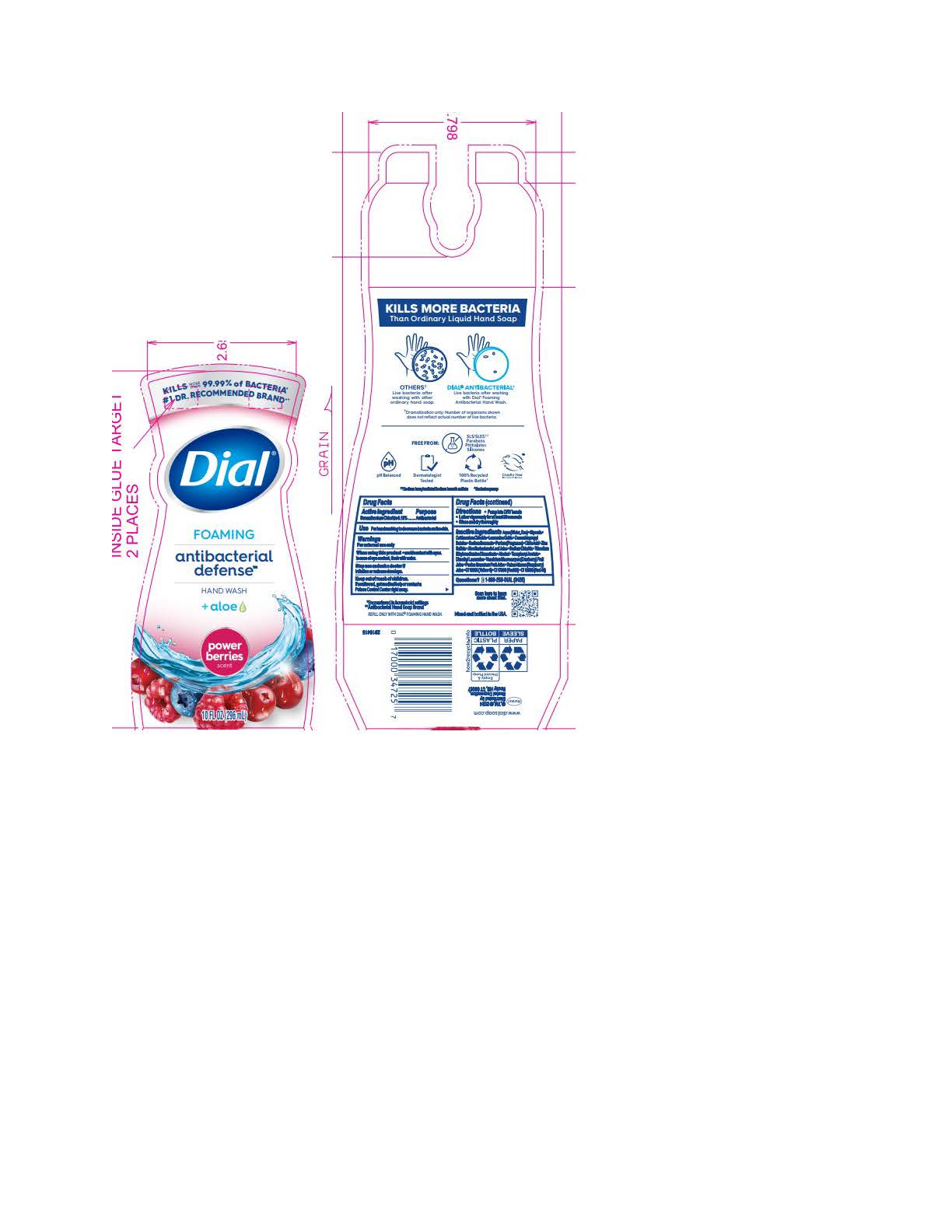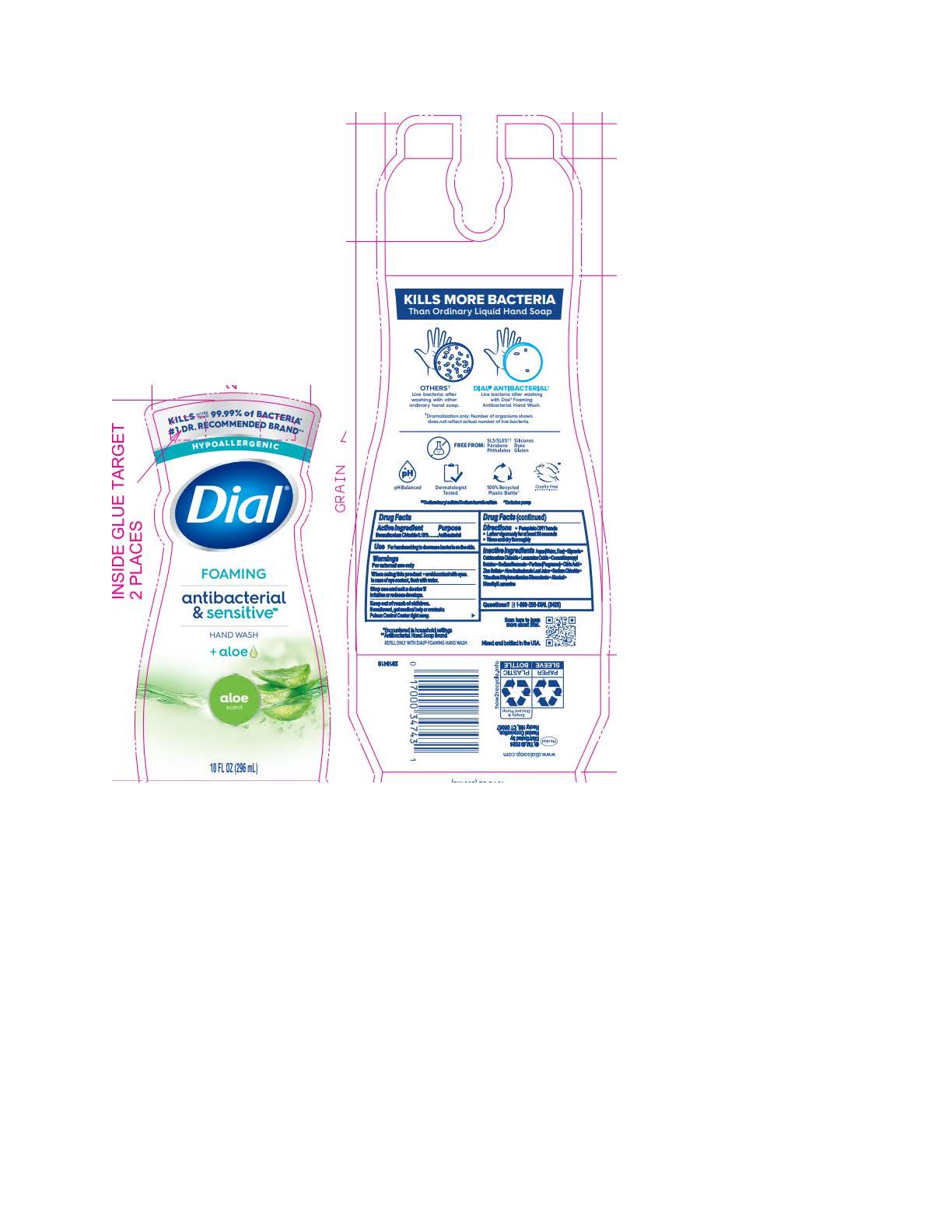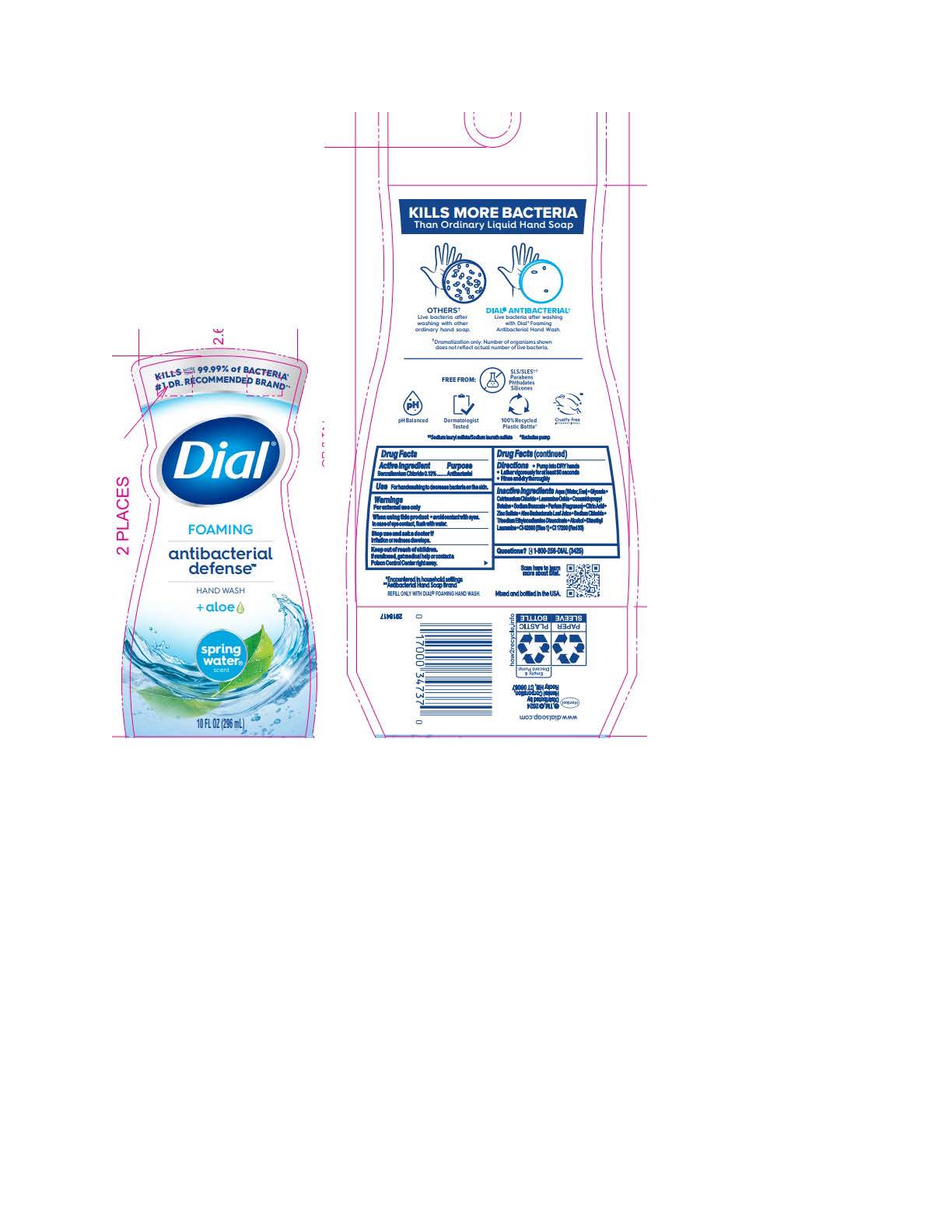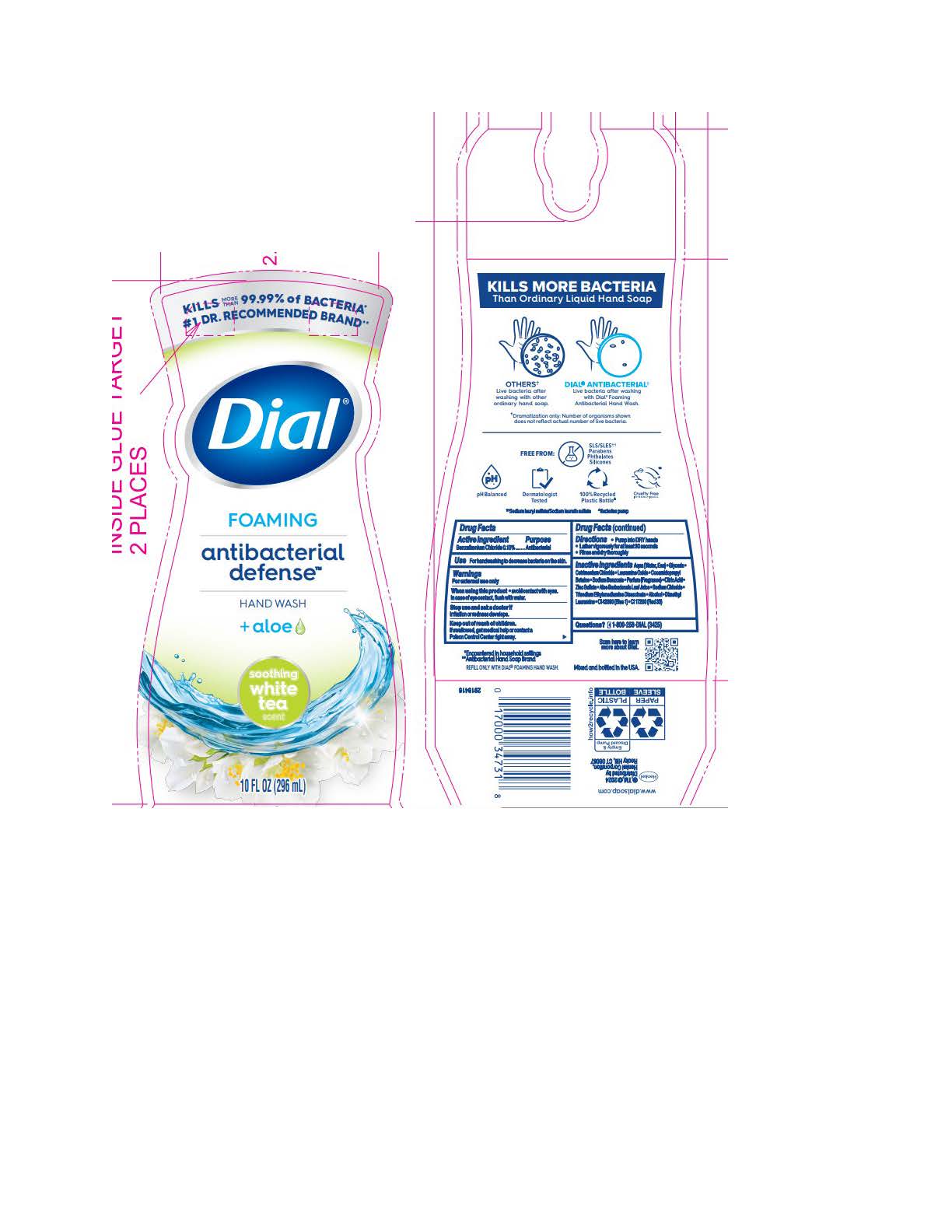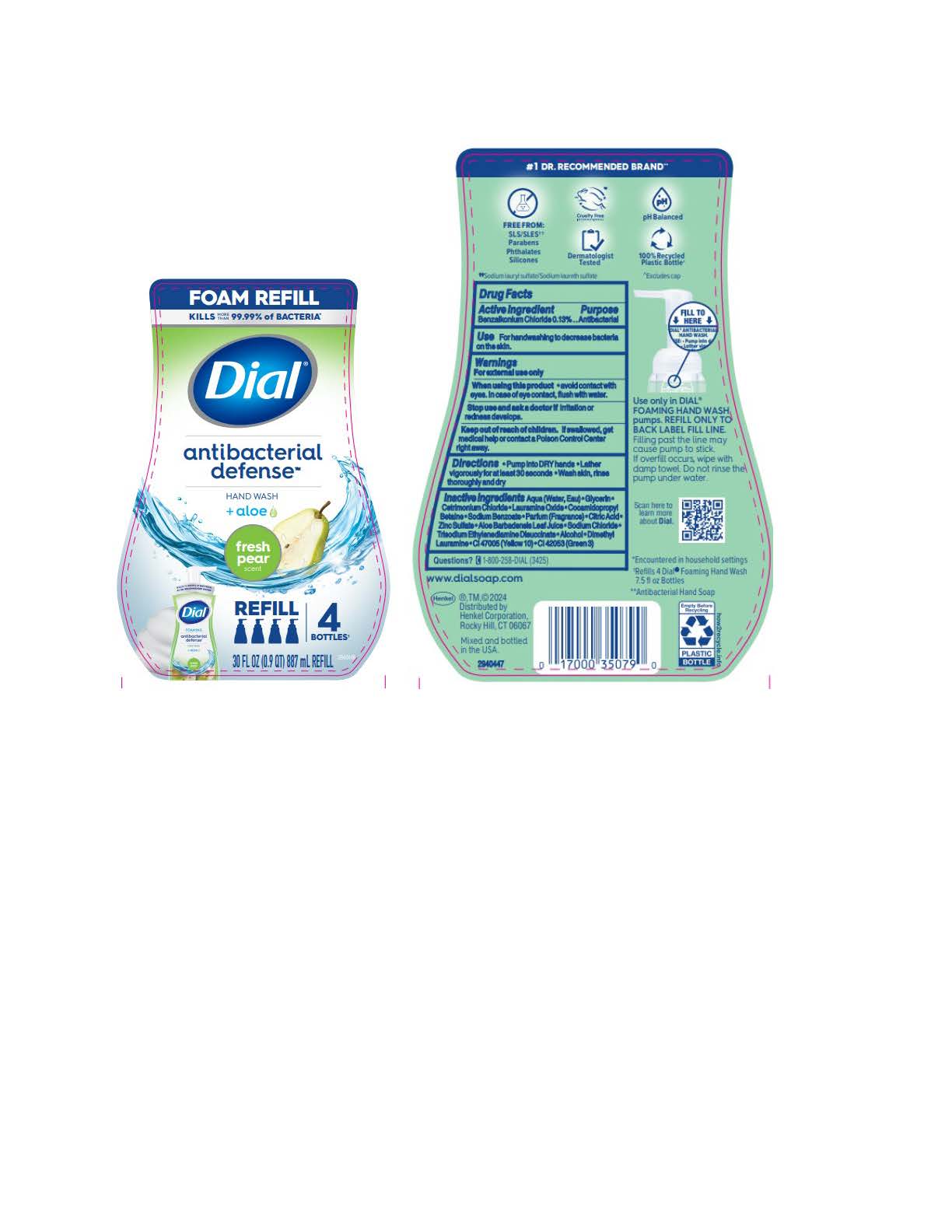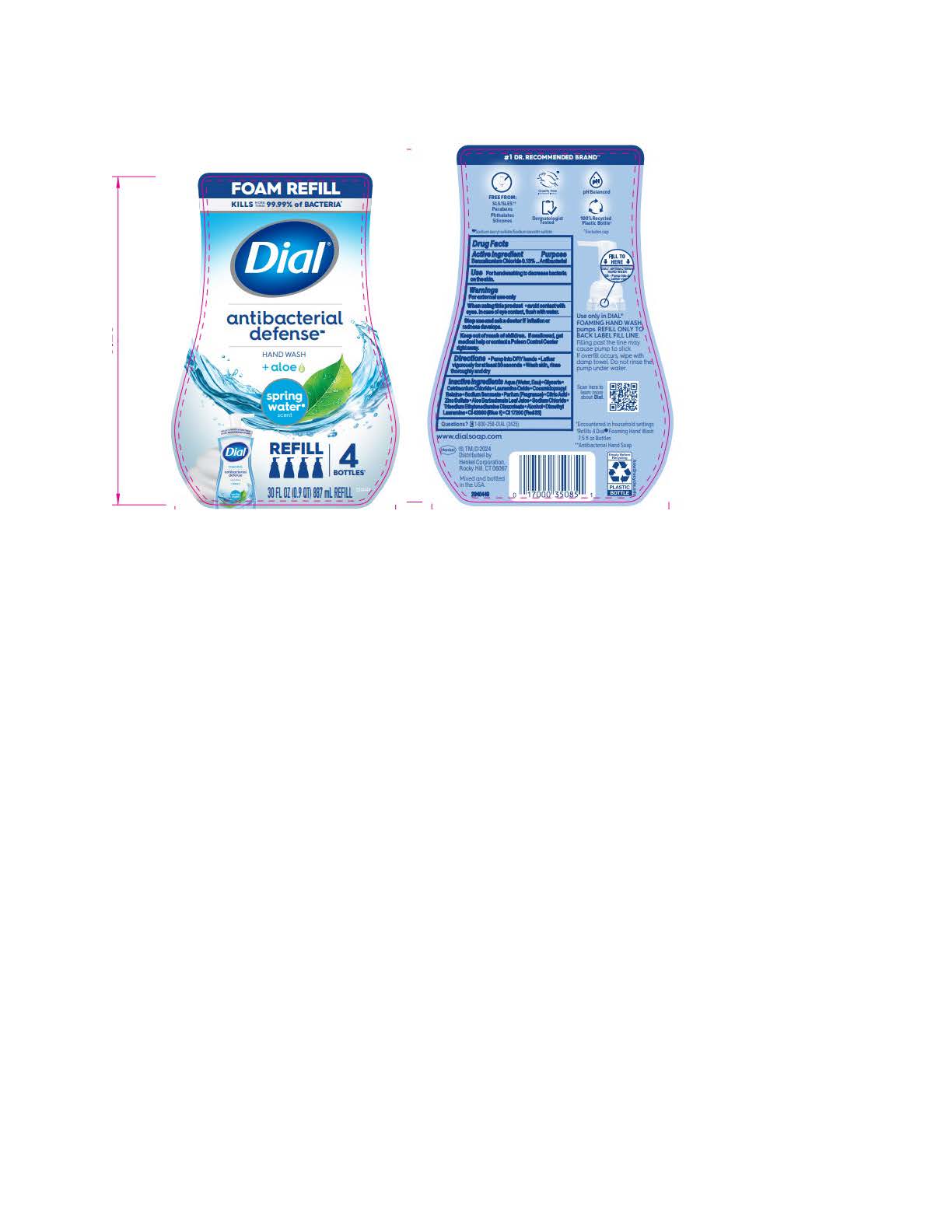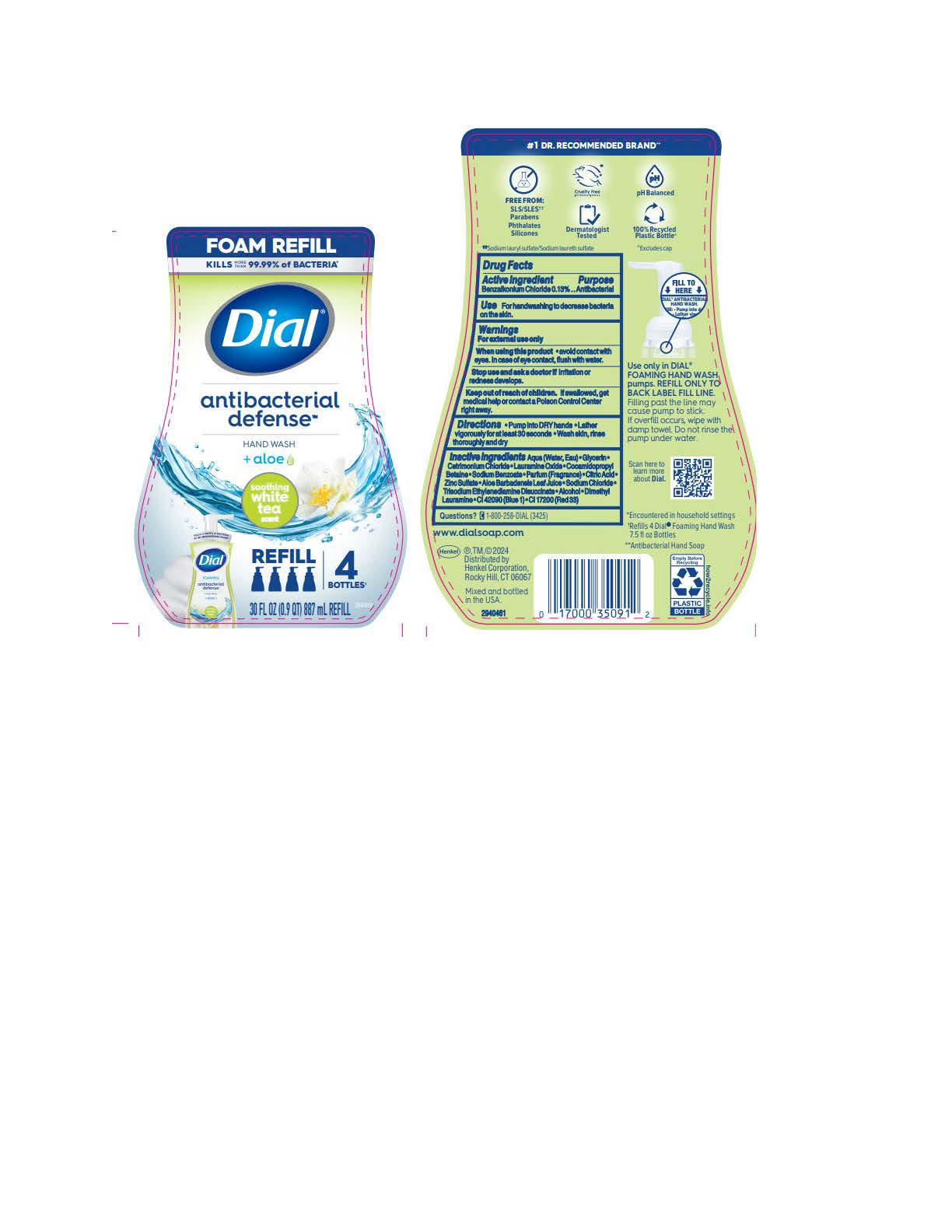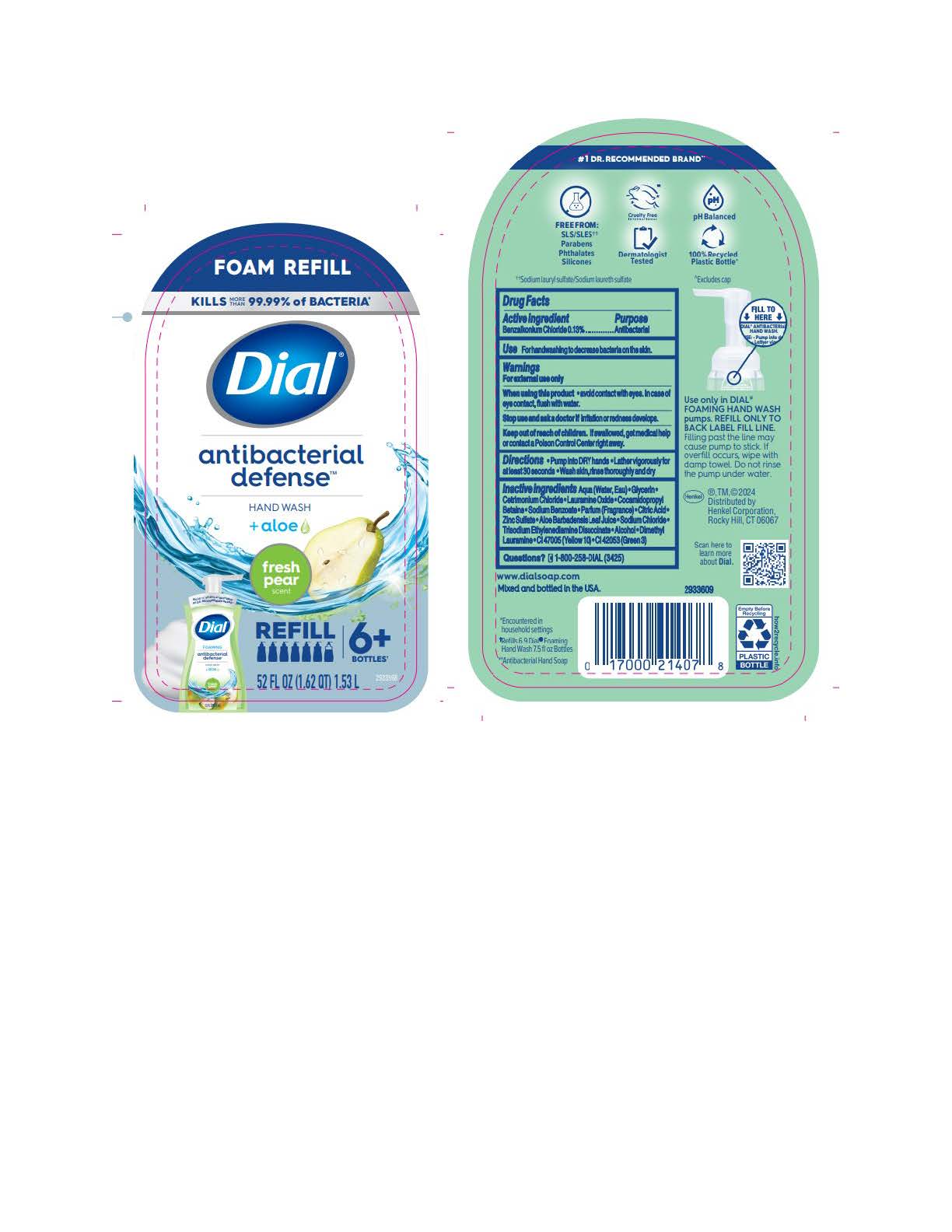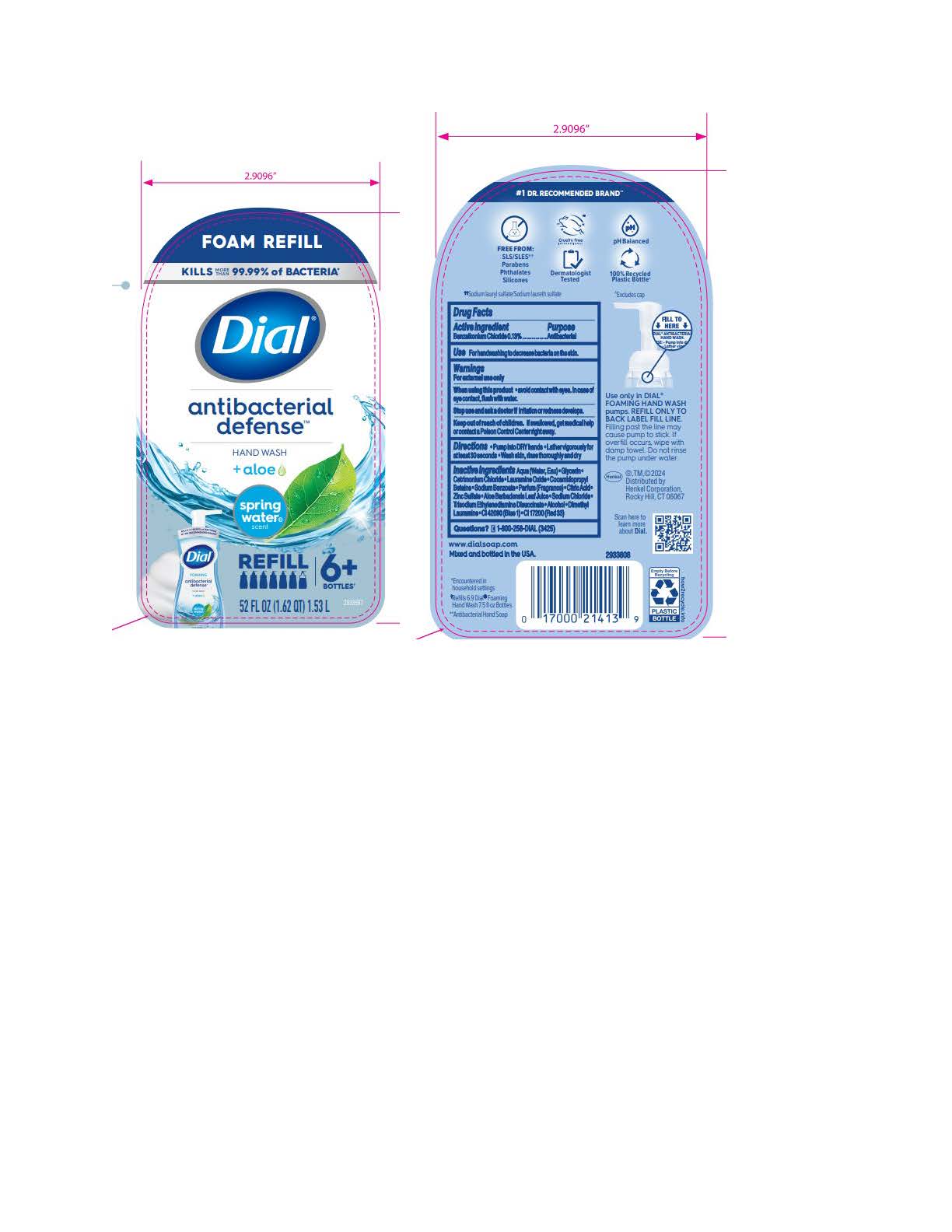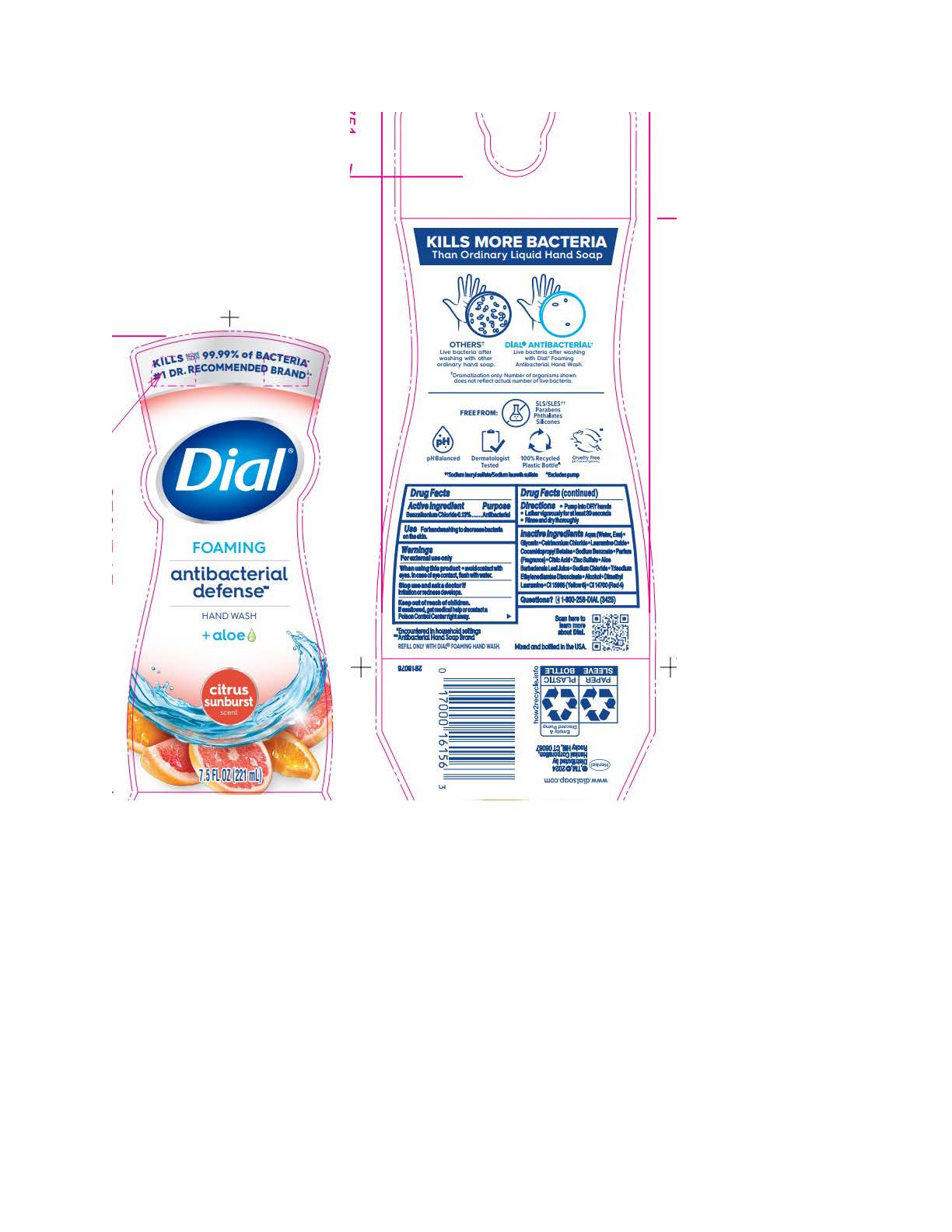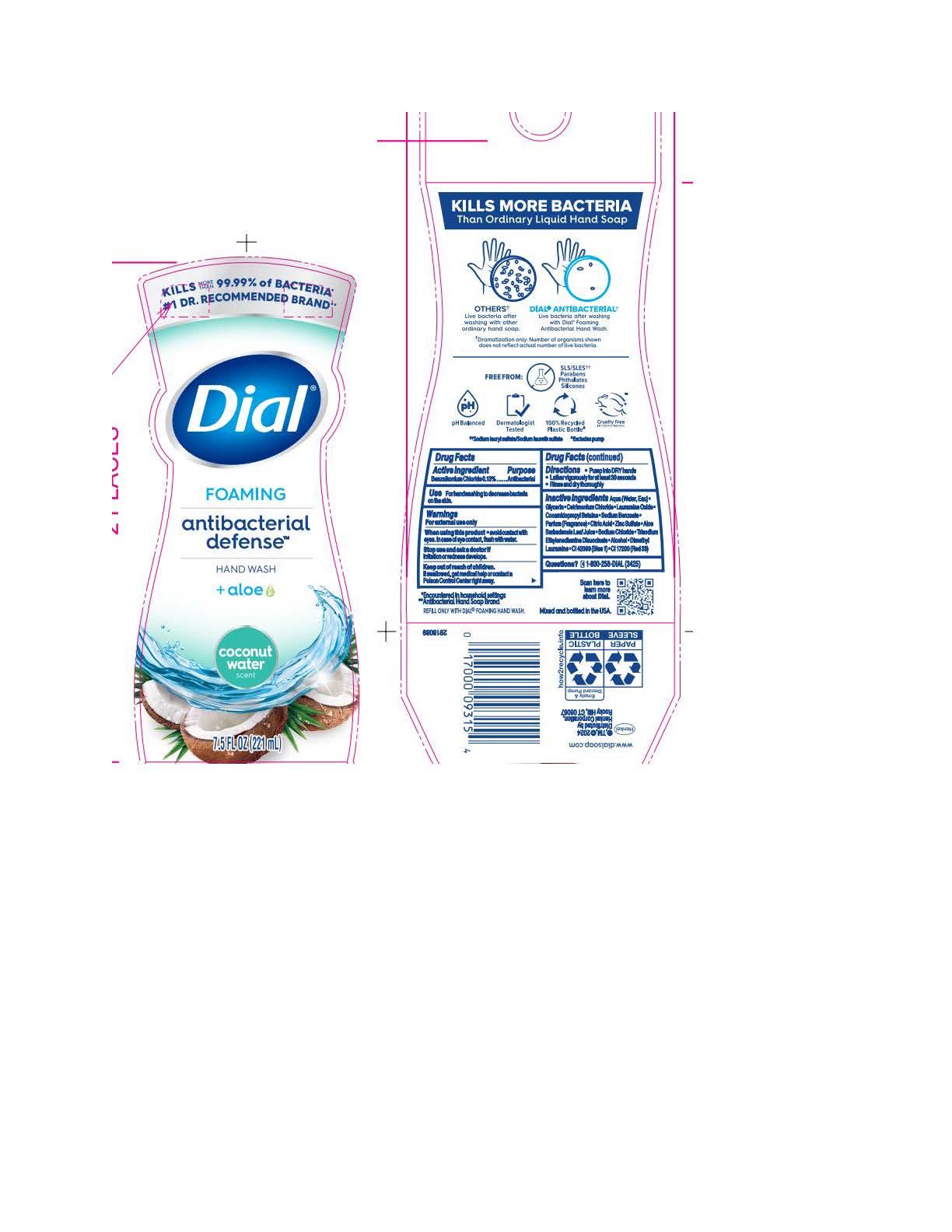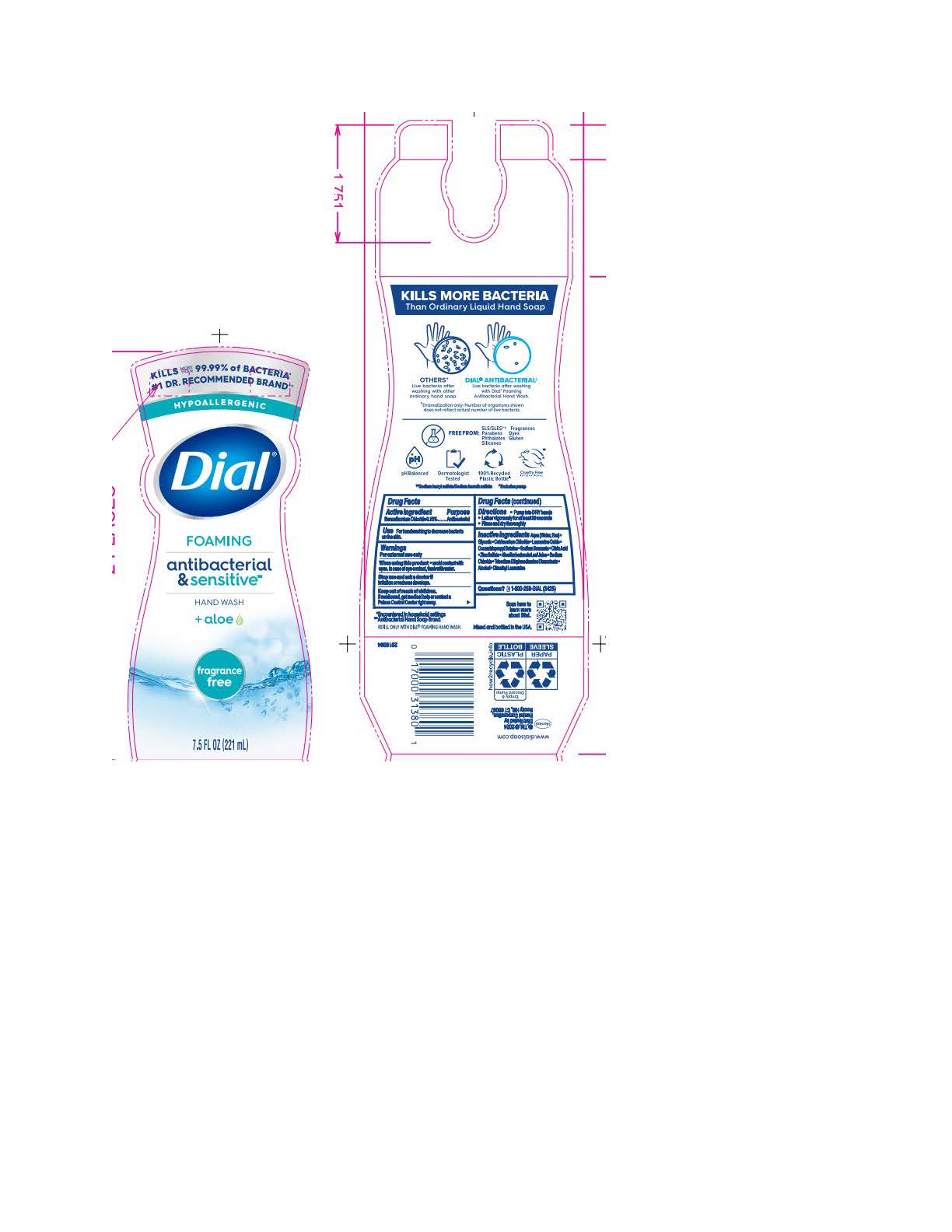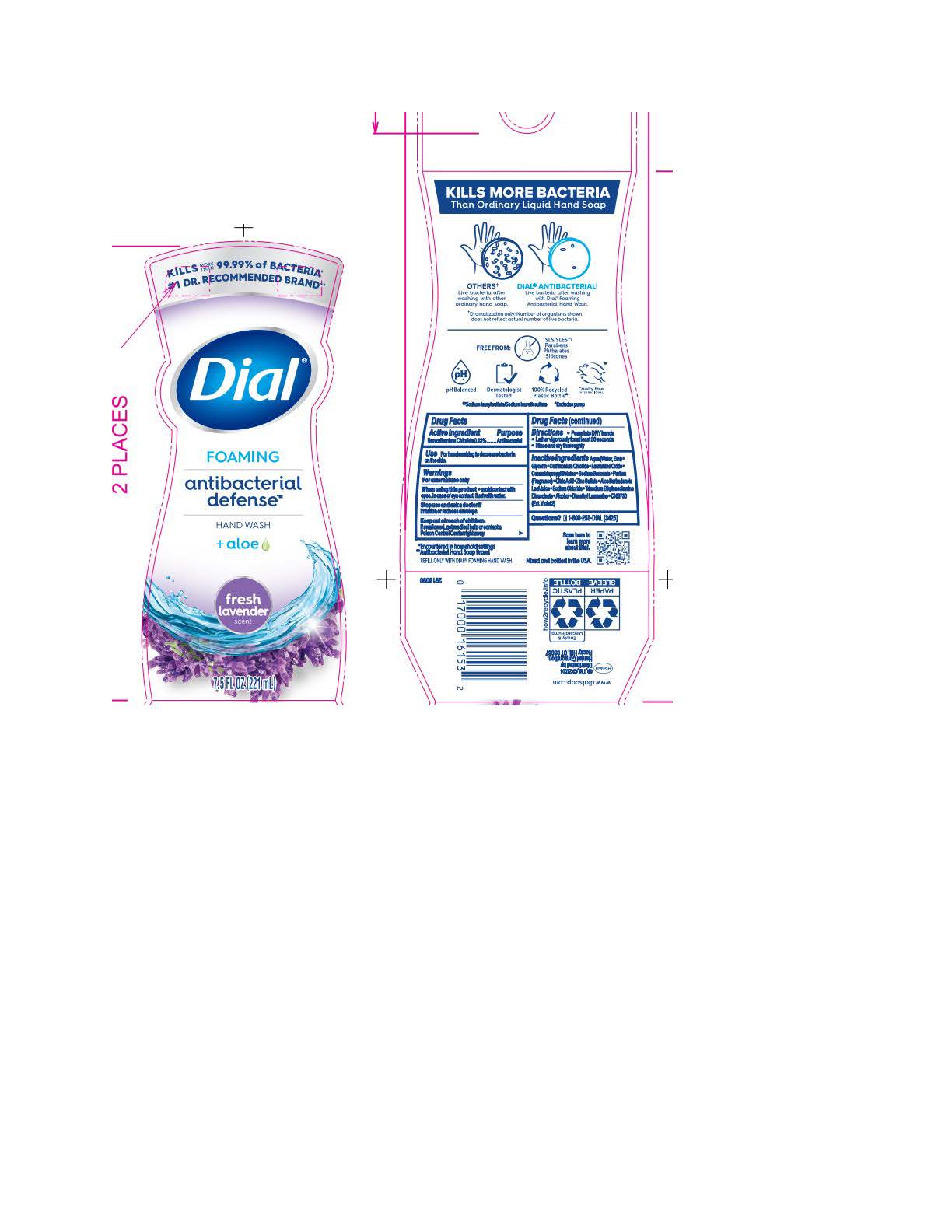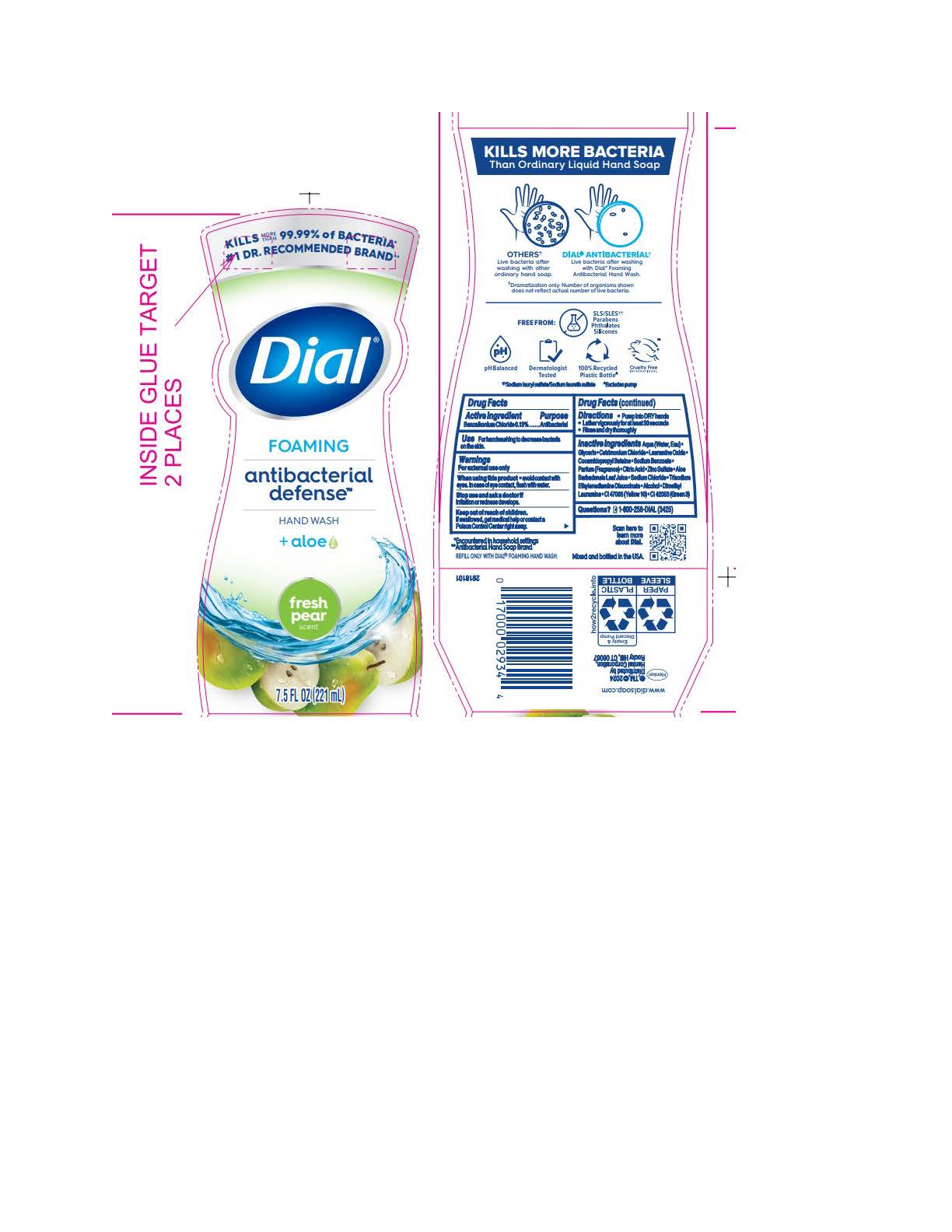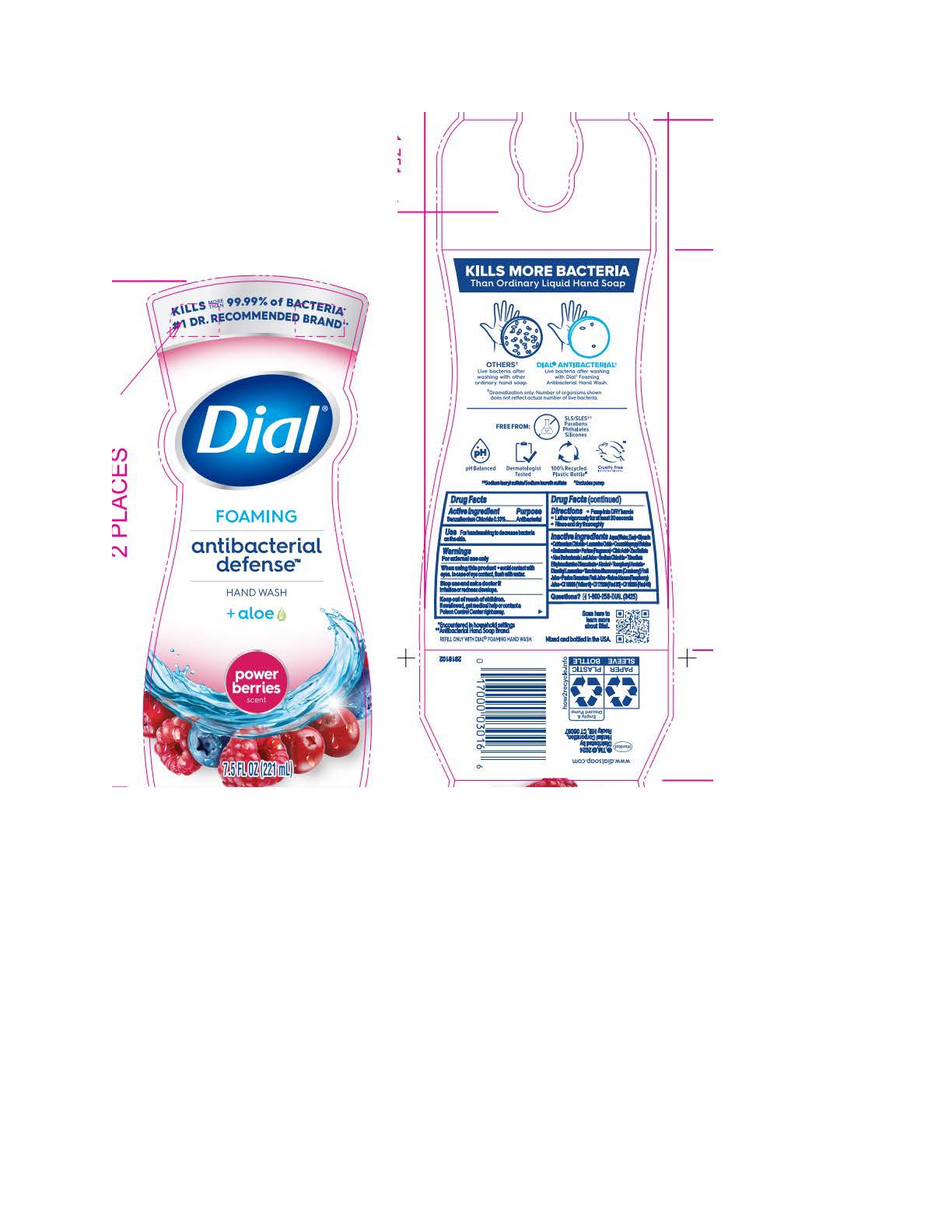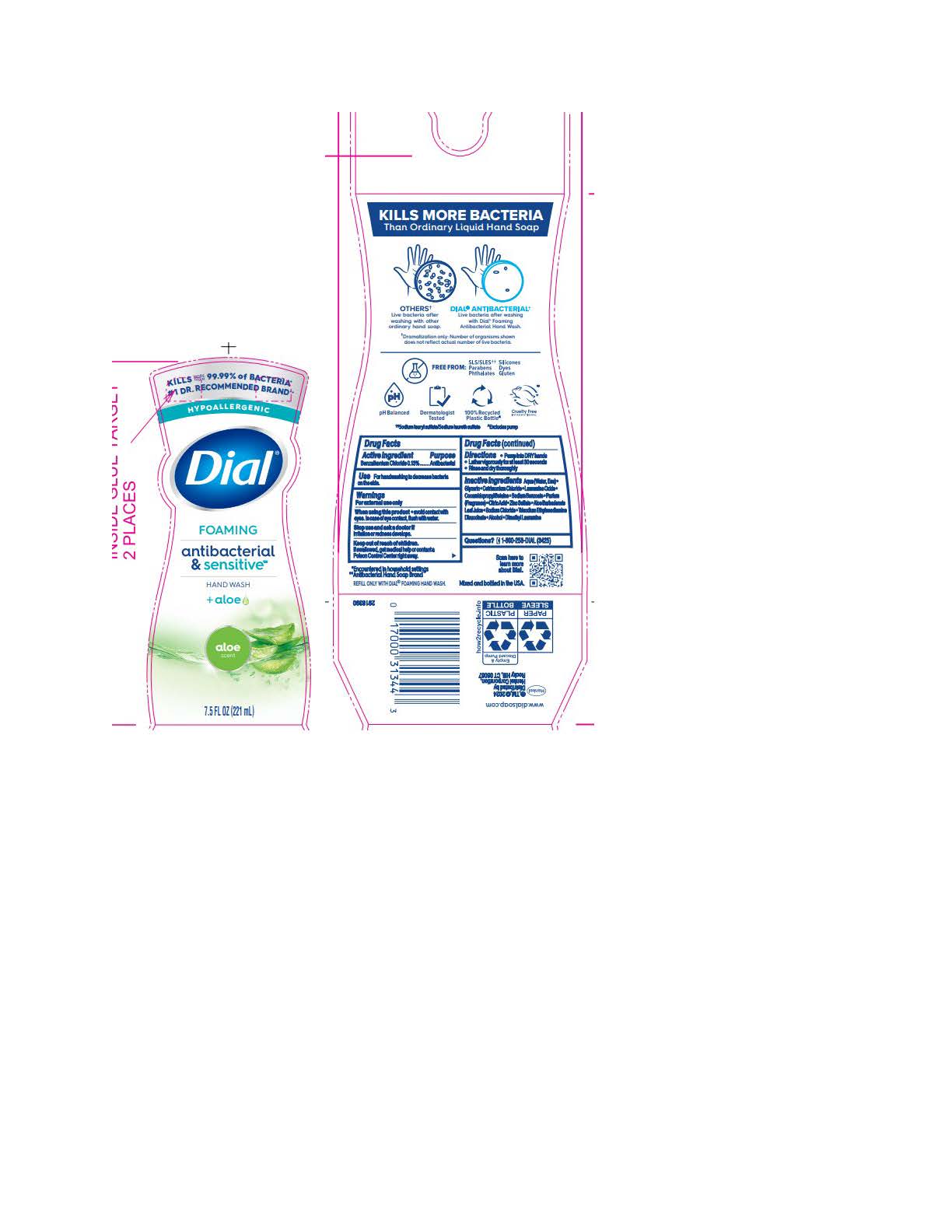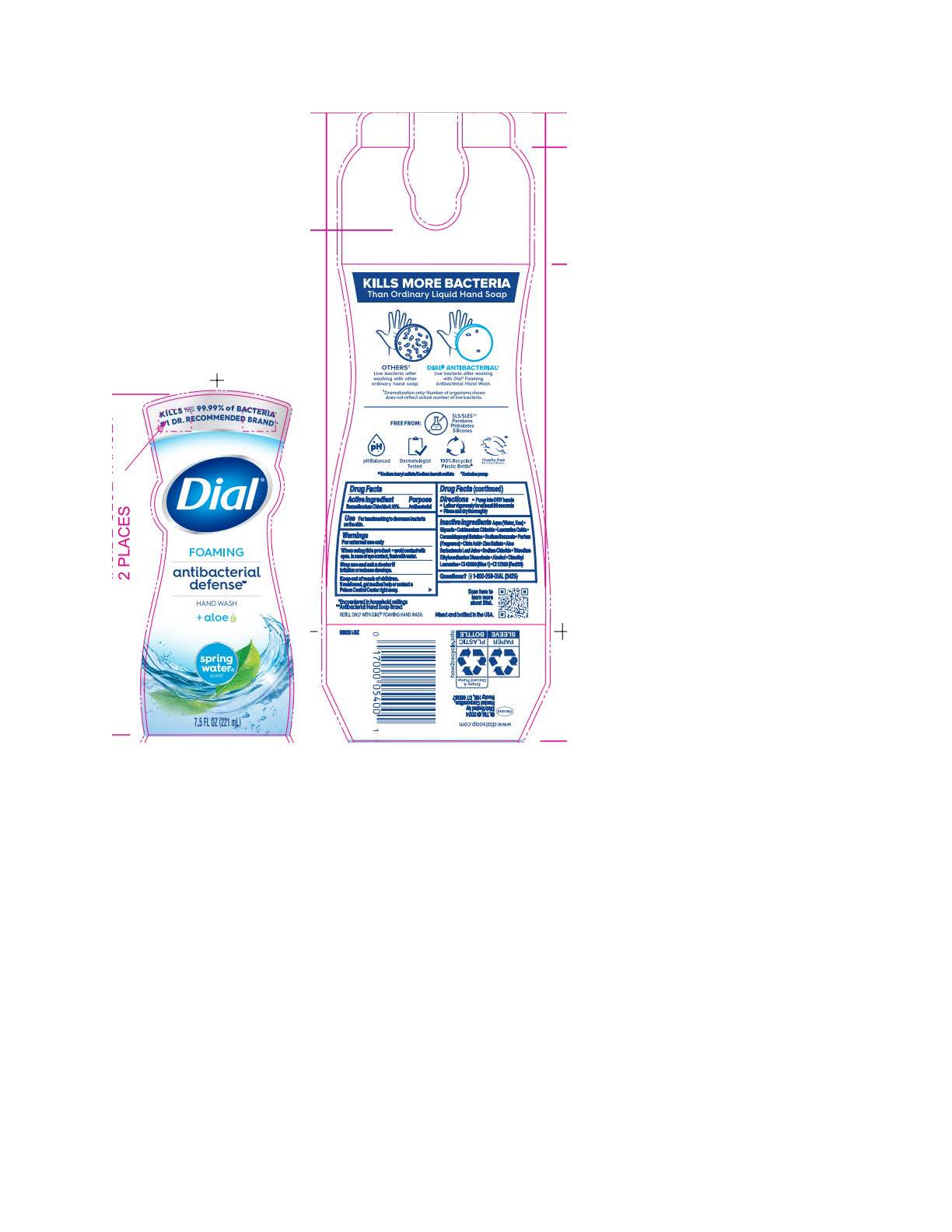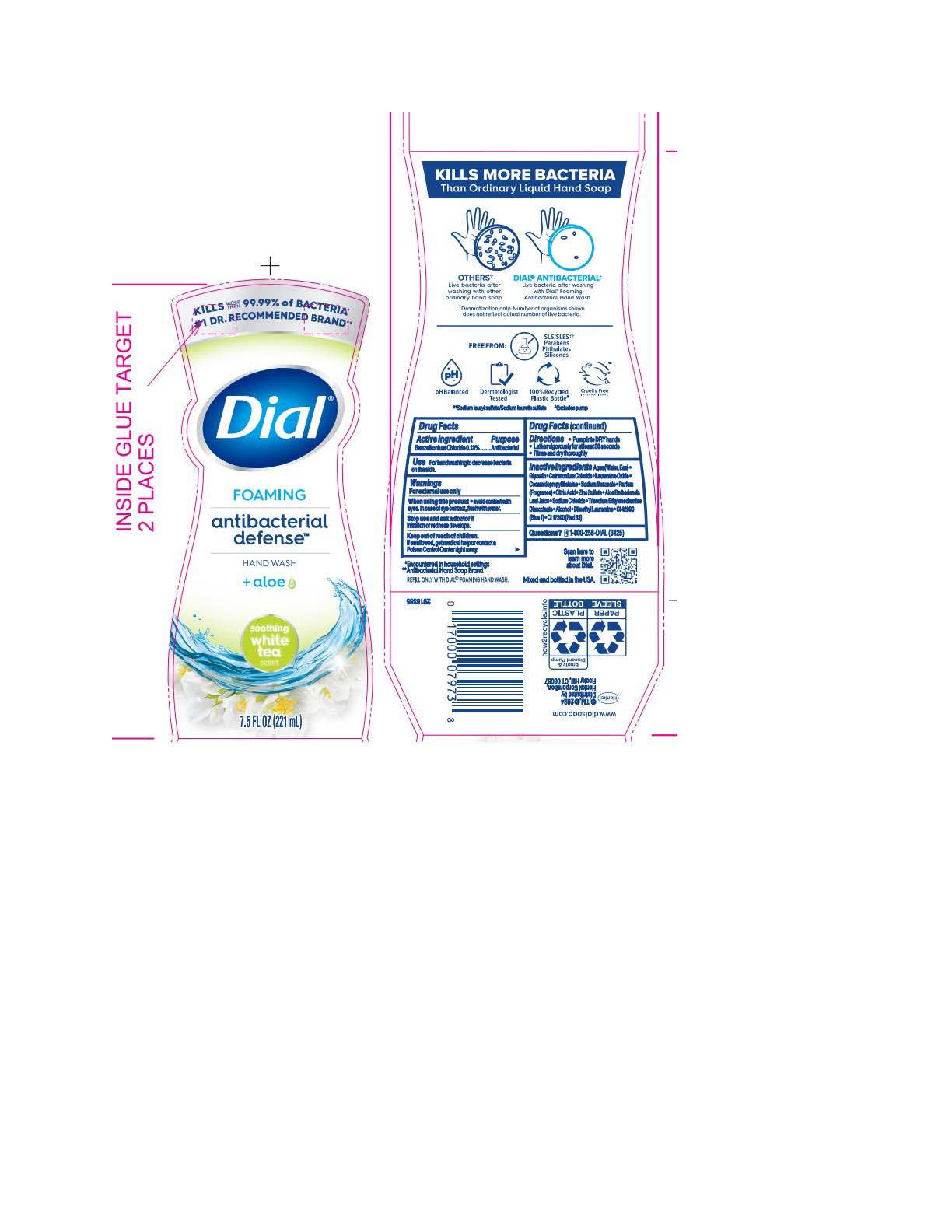 DRUG LABEL: Dial Foaming Antibacterial Defense Soothing White Tea
NDC: 54340-186 | Form: SOLUTION
Manufacturer: Henkel Corporation
Category: otc | Type: HUMAN OTC DRUG LABEL
Date: 20251106

ACTIVE INGREDIENTS: BENZALKONIUM CHLORIDE 0.13 g/100 mL
INACTIVE INGREDIENTS: DIMETHYL LAURAMINE 0.0099 g/100 mL; WATER 95.627 g/100 mL; GLYCERIN 1.512 g/100 mL; CETRIMONIUM CHLORIDE 0.999 g/100 mL; LAURAMINE OXIDE 0.597 g/100 mL; COCAMIDOPROPYL BETAINE 0.391 g/100 mL; SODIUM BENZOATE 0.2 g/100 mL; CITRIC ACID MONOHYDRATE 0.11 g/100 mL; ZINC SULFATE 0.1 g/100 mL; ALOE VERA LEAF 0.0997 g/100 mL; SODIUM CHLORIDE 0.072 g/100 mL; TRISODIUM ETHYLENEDIAMINE DISUCCINATE 0.0185 g/100 mL; ALCOHOL 0.013 g/100 mL; FD&C BLUE NO. 1 0.000009 g/100 mL; D&C RED NO. 33 0.000008 g/100 mL

Dial Foaming Antibacterial Defense Hand Wash
Dial Antibacterial Foaming Hand Wash
Dial Foam Refill Antibacterial Defense Hand Wash
Dial Foaming Antibacterial Defense Hand Wash Fresh Pear
Dial Foaming Antibacterial Defense Hand Wash Soothing White Tea
Dial Foaming Antibacterial Defense Hand Wash Coconut Water
Dial Foaming Antibacterial Defense Hand Wash Spring Water
Dial Foaming Antibacterial Defense Hand Wash Power Berries
Dial Foaming Antibacterial Defense Hand Wash Fresh Lavender
Dial Foaming Antibacterial Defense Hand Wash Citrus Sunburst
Dial Foaming Antibacterial & Sensitive Hand Wash Aloe
Dial Foaming Antibacterial & Sensitive Hand Wash Fragrance Free

Active Ingredient

Benzalkonium Chloride 0.13%

Purpose

Antibacterial

Uses

For Handwashing to decreases bacteria on the skin.

Warnings

For external use only.

When Using this Product

Avoid Contact with eyes. In case of eye contact, flush with water.

Stop use and ask doctor if

Irritation or redness develops

Keep out of reach of children.

If swallowed get medical help or contact a Poison Control Center right away.

Directions

- Pump into hands, wet as needed.
- Lather vigorously for at least 30 seconds.
- Wash skin, rinse thoroughly and dry.

Inactive Ingredients

Fresh Lavender

Aqua (Water, Eau) · Glycerin · Cetrimonium Chloride · Lauramine Oxide · Cocamidopropyl Betaine · Sodium Benzoate ·
Parfum (Fragrance) · Citric Acid · Zinc Sulfate · Aloe Barbadensis Leaf Juice · Sodium Chloride · Trisodium Ethylenediamine Disuccinate · Alcohol · Dimethyl Lauramine · CI 60730 (Ext. Violet 2)

Coconut Water

Inactive ingredients: Aqua (Water, Eau) · Glycerin · Cetrimonium Chloride · Lauramine Oxide · Cocamidopropyl Betaine · Sodium Benzoate · Parfum (Fragrance) · Citric Acid · Zinc Sulfate · Aloe Barbadensis Leaf Juice · Sodium Chloride · Trisodium Ethylenediamine Disuccinate · Alcohol · Dimethyl Lauramine · CI 42090 (Blue 1) · CI 17200 (Red 33)

Fresh Pear

Inactive ingredients: Aqua (Water, Eau) · Glycerin · Cetrimonium Chloride · Lauramine Oxide · Cocamidopropyl Betaine · Sodium Benzoate · Parfum (Fragrance) · Citric Acid · Zinc Sulfate · Aloe Barbadensis Leaf Juice · Sodium Chloride · Trisodium Ethylenediamine Disuccinate · Alcohol · Dimethyl Lauramine · CI 47005 (Yellow 10) · CI 42053 (Green 3)

Soothing White Tea

Aqua (Water, Eau) · Glycerin · Cetrimonium Chloride · Lauramine Oxide · Cocamidopropyl Betaine · Sodium Benzoate ·
Parfum (Fragrance) · Citric Acid · Zinc Sulfate · Aloe Barbadensis Leaf Juice · Sodium Chloride · Trisodium Ethylenediamine Disuccinate · Alcohol · Dimethyl Lauramine · CI 42090 (Blue 1) · CI 17200 (Red 33)

Sensitive Aloe

Inactive ingredients: Aqua (Water, Eau) · Glycerin · Cetrimonium Chloride · Lauramine Oxide · Cocamidopropyl Betaine · Sodium Benzoate · Parfum (Fragrance) · Citric Acid · Zinc Sulfate · Aloe Barbadensis Leaf Juice · Sodium Chloride · Trisodium Ethylenediamine Disuccinate · Alcohol · Dimethyl Lauramine

Citrus Sunburst

Aqua (Water, Eau) · Glycerin · Cetrimonium Chloride · Lauramine Oxide · Cocamidopropyl Betaine · Sodium Benzoate ·
Parfum (Fragrance) · Citric Acid · Zinc Sulfate · Aloe Barbadensis Leaf Juice · Sodium Chloride · Trisodium Ethylenediamine Disuccinate · Alcohol · Dimethyl Lauramine · CI 15985 (Yellow 6) · CI 14700 (Red 4)

Power Berries

Aqua (Water, Eau) · Glycerin · Cetrimonium Chloride · Lauramine Oxide · Cocamidopropyl Betaine · Sodium Benzoate ·
Parfum (Fragrance) · Citric Acid · Zinc Sulfate · Aloe Barbadensis Leaf Juice · Sodium Chloride · Trisodium Ethylenediamine Disuccinate · Alcohol · Tocopheryl Acetate · Dimethyl Lauramine · Vaccinium Macrocarpon (Cranberry) Fruit Juice · Punica Granatum Fruit Juice · Rubus Idaeus (Raspberry) Juice · CI 15985 (Yellow 6) · CI 17200 (Red 33) · CI 16035 (Red 40)

Spring Water

Aqua (Water, Eau) · Glycerin · Cetrimonium Chloride · Lauramine Oxide · Cocamidopropyl Betaine · Sodium Benzoate · Parfum (Fragrance) · Citric Acid · Zinc Sulfate · Aloe Barbadensis Leaf Juice · Sodium Chloride · Trisodium Ethylenediamine Disuccinate · Alcohol · Dimethyl Lauramine · CI 42090 (Blue 1) · CI 17200 (Red 33)

Sensitive & Fragrance Free

Aqua (Water, Eau) · Glycerin · Cetrimonium Chloride · Lauramine Oxide · Cocamidopropyl Betaine · Sodium Benzoate ·
Citric Acid · Zinc Sulfate · Aloe Barbadensis Leaf Juice · Sodium Chloride · Trisodium Ethylenediamine Disuccinate · Alcohol · Dimethyl Lauramine

Questions

call 1-800-258-DIAL(3425)

Legal Entity

www.dialsoap.com

henkel Bean Logo

R,TM,c2024 Distributed by

Henkel Corporation,Rocky Hill, CT 06067

^Encountered in household settings

#Antibacterial Hand Soap

Indications & Usage

For handwasing to decrease bacteria on the skin.

Topical Liquid

Foaming Hand Wash